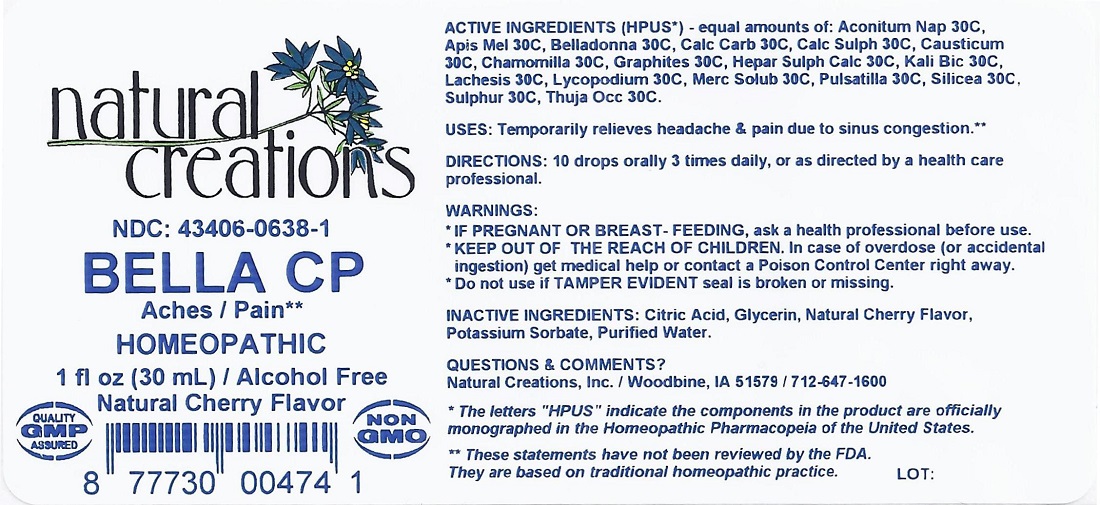 DRUG LABEL: BELLA CP
NDC: 43406-0638 | Form: LIQUID
Manufacturer: Natural Creations, Inc.
Category: homeopathic | Type: HUMAN OTC DRUG LABEL
Date: 20160928

ACTIVE INGREDIENTS: ACONITUM NAPELLUS 30 [hp_C]/1 mL; APIS MELLIFERA 30 [hp_C]/1 mL; ATROPA BELLADONNA 30 [hp_C]/1 mL; OYSTER SHELL CALCIUM CARBONATE, CRUDE 30 [hp_C]/1 mL; CALCIUM SULFATE ANHYDROUS 30 [hp_C]/1 mL; CAUSTICUM 30 [hp_C]/1 mL; MATRICARIA RECUTITA 30 [hp_C]/1 mL; GRAPHITE 30 [hp_C]/1 mL; CALCIUM SULFIDE 30 [hp_C]/1 mL; POTASSIUM DICHROMATE 30 [hp_C]/1 mL; LACHESIS MUTA VENOM 30 [hp_C]/1 mL; LYCOPODIUM CLAVATUM SPORE 30 [hp_C]/1 mL; MERCURIUS SOLUBILIS 30 [hp_C]/1 mL; ANEMONE PULSATILLA 30 [hp_C]/1 mL; SILICON DIOXIDE 30 [hp_C]/1 mL; SULFUR 30 [hp_C]/1 mL; THUJA OCCIDENTALIS LEAFY TWIG 30 [hp_C]/1 mL
INACTIVE INGREDIENTS: CITRIC ACID ACETATE; GLYCERIN; POTASSIUM SORBATE; WATER

BELLA CP

ACTIVE INGREDIENT

ACTIVE INGREDIENTS (HPUS*) - equal amounts of: Aconitum Nap 30C, Apis Mel 30C, Belladonna 30C, Calc Carb 30C, Calc Sulph 30C, Causticum 30C, Chamomilla 30C, Graphites 30C, Hepar Sulph Calc 30C, Kali Bic 30C, Lachesis 30C, Lycopodium 30C, Merc Solub 30C, Pulsatilla 30C, Silicea 30C, Sulphur 30C, Thuja Occ 30C.

PURPOSE

USES: Temporarily relieves headache & pain due to sinus congestion.**

INDICATIONS AND USAGE

USES: Temporarily relieves headache & pain due to sinus congestion.**

DOSAGE AND ADMINISTRATION

DIRECTIONS: 10 drops orally 3 times daily, or as directed by a health care professional.

WARNINGS:

* IF PREGNANT OR BREAST-FEEDING, ask a health care professional before use.

* KEEP OUT OF THE REACH OF CHILDREN. In case of overdose (or accidental ingestion) get medical help or contact a Poison Control Center right away.

* Do not use if TAMPER EVIDENT seal is broken or missing.

KEEP OUT OF REACH OF CHILDREN

KEEP OUT OF THE REACH OF CHILDREN. In case of overdose (or accidental ingestion) get medical help or contact a Poison Control Center right away.

INACTIVE INGREDIENT

INACTIVE INGREDIENTS: Citric Acid, Glycerin, Natural Cherry Flavor, Potassium Sorbate, Purified Water.

QUESTIONS & COMMENTS?

Natural Creations, Inc. / Woodbine, IA 51579 / 712-647-1600

REFERENCES

* The letters "HPUS" indicate the components in the product are officially monographed in the Homeopathic Pharmacopeia of the United States.

** These statements have not been reviewed by the FDA. They are based on traditional homeopathic practice.

LOT:

PACKAGE LABEL

NDC: 43406-0638-1

BELLA CP

Aches / Pain**

HOMEOPATHIC

1 fl oz (30 mL) / Alcohol Free

Natural Cherry Flavor

GMP Logo UPC: 877730004741 NON GMO Logo